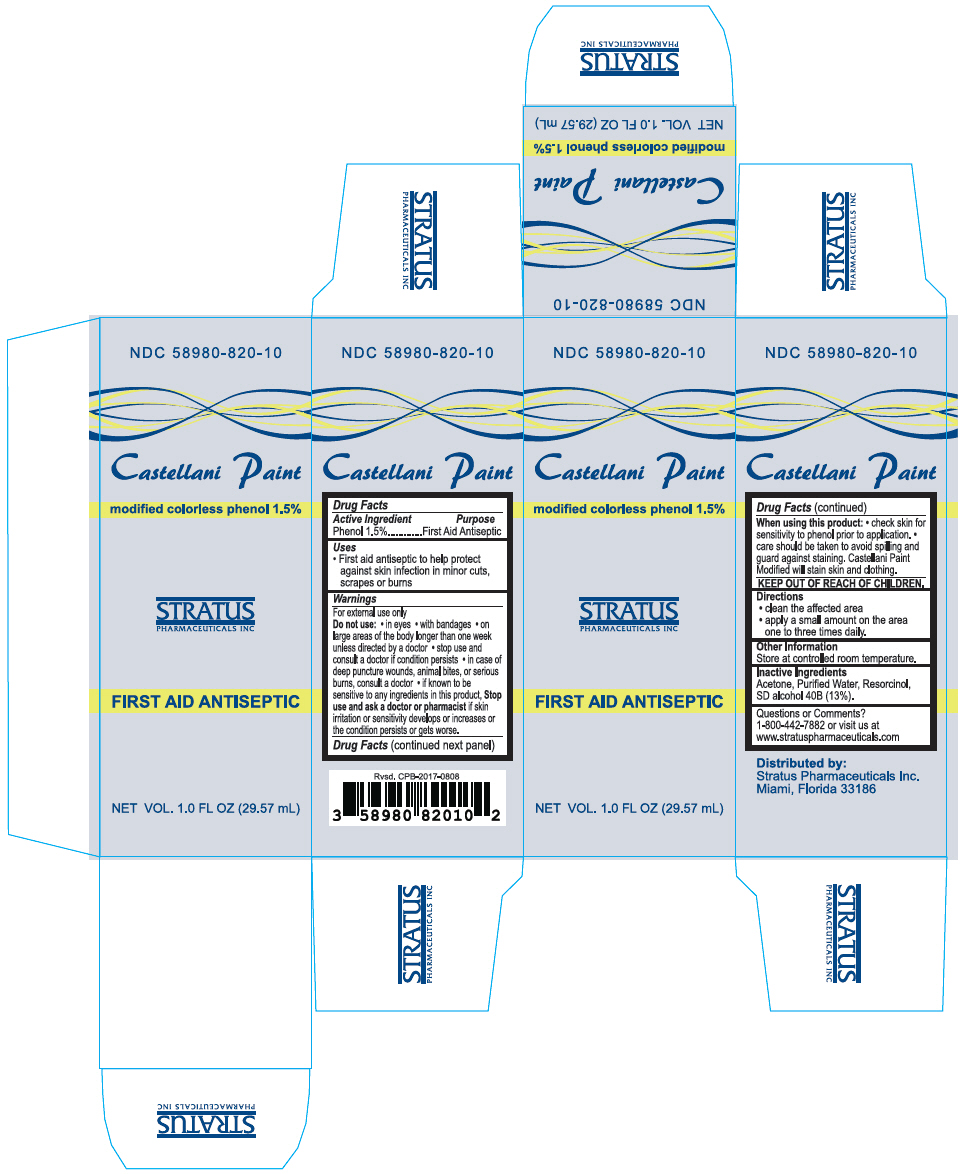 DRUG LABEL: Castellani Paint
NDC: 58980-820 | Form: LIQUID
Manufacturer: Stratus Pharamceuticals
Category: otc | Type: HUMAN OTC DRUG LABEL
Date: 20251030

ACTIVE INGREDIENTS: Phenol 15 mg/1 mL
INACTIVE INGREDIENTS: Water; ACETONE; RESORCINOL; ALCOHOL

Castellani Paint

Drug Facts

Active Ingredient

Phenol 1.5%

Purpose

First Aid Antiseptic

Uses

- First aid antiseptic to help protect against skin infection in minor cuts, scrapes or burns

Warnings

For external use only

Do not use

- in eyes
- with bandages
- on large areas of the body longer than one week unless directed by a doctor
- stop use and consult a doctor if condition persists
- in case of deep puncture wounds, animal bites, or serious burns, consult a doctor
- if known to be sensitive to any ingredients in this product,

Stop use and ask a doctor or pharmacist if skin irritation or sensitivity develops or increases or the condition persists or gets worse.

When using this product

- check skin for sensitivity to phenol prior to application.
- care should be taken to avoid spilling and guard against staining. Castellani Paint Modified will stain skin and clothing.

KEEP OUT OF REACH OF CHILDREN.

Directions

- clean the affected area
- apply a small amount on the area one to three times daily.

Other Information

Store at controlled room temperature.

Inactive Ingredients

Acetone, Purified Water, Resorcinol, SD alcohol 40B (13%).

Questions or Comments?

1-800-442-7882 or visit us at www.stratuspharmaceuticals.com

Distributed by:
Stratus Pharmaceuticals Inc.
Miami, Florida 33186

PRINCIPAL DISPLAY PANEL - 29.57 mL Bottle Box

NDC 58980-820-10

Castellani Paint

modified colorless phenol 1.5%

STRATUS
PHARMACEUTICALS INC

FIRST AID ANTISEPTIC

NET VOL. 1.0 FL OZ (29.57 mL)